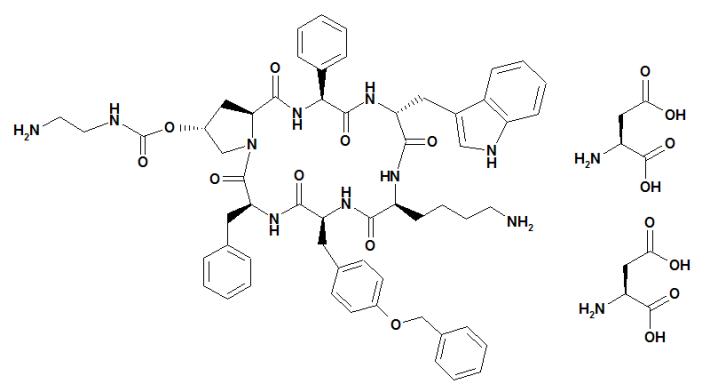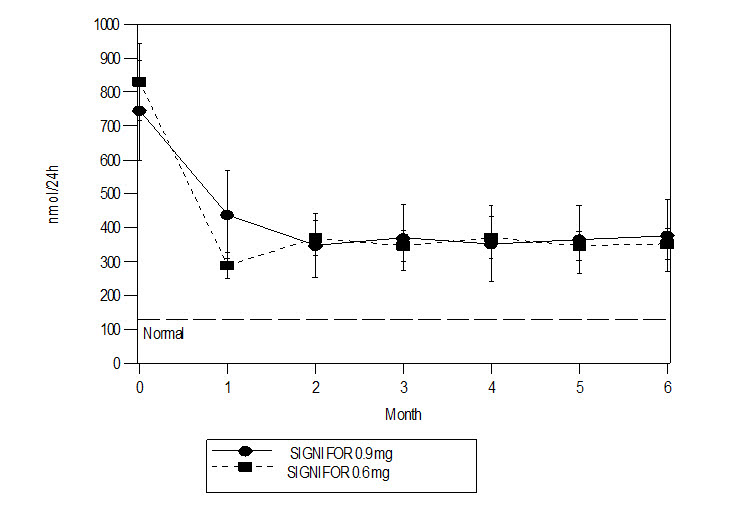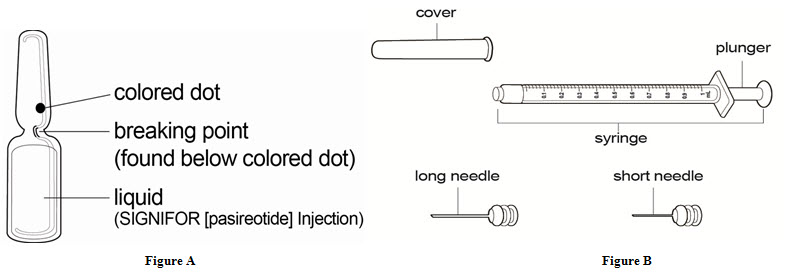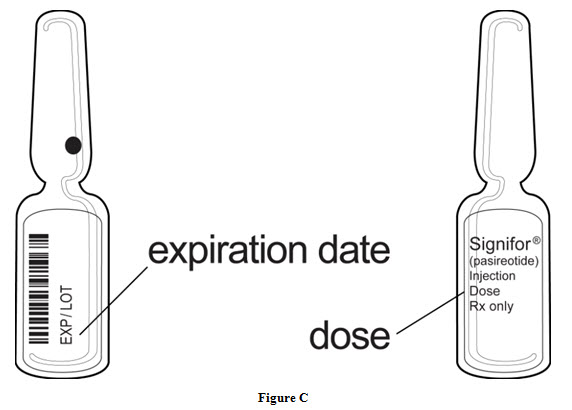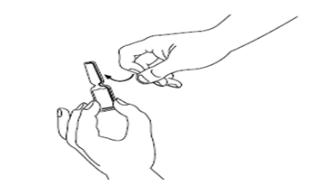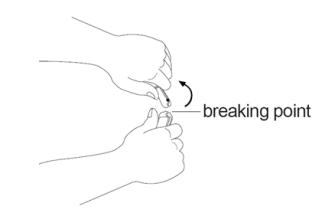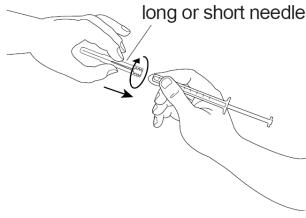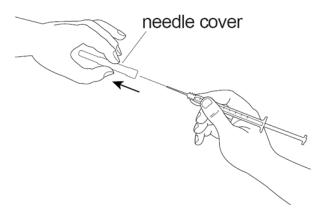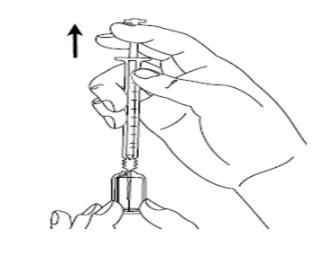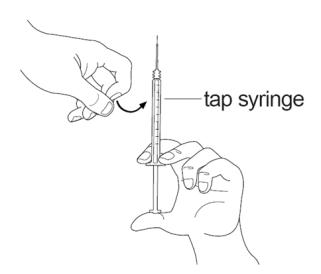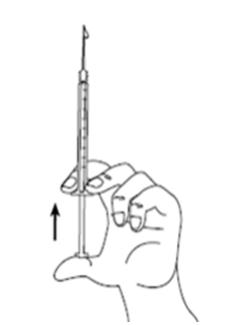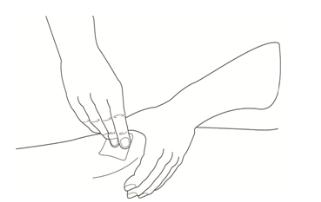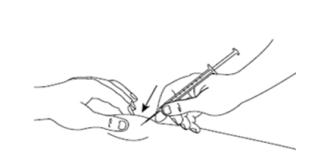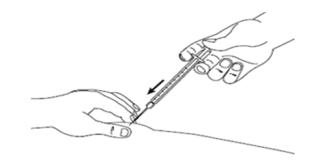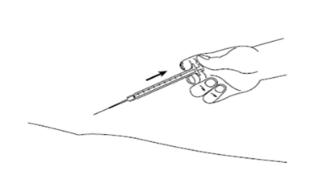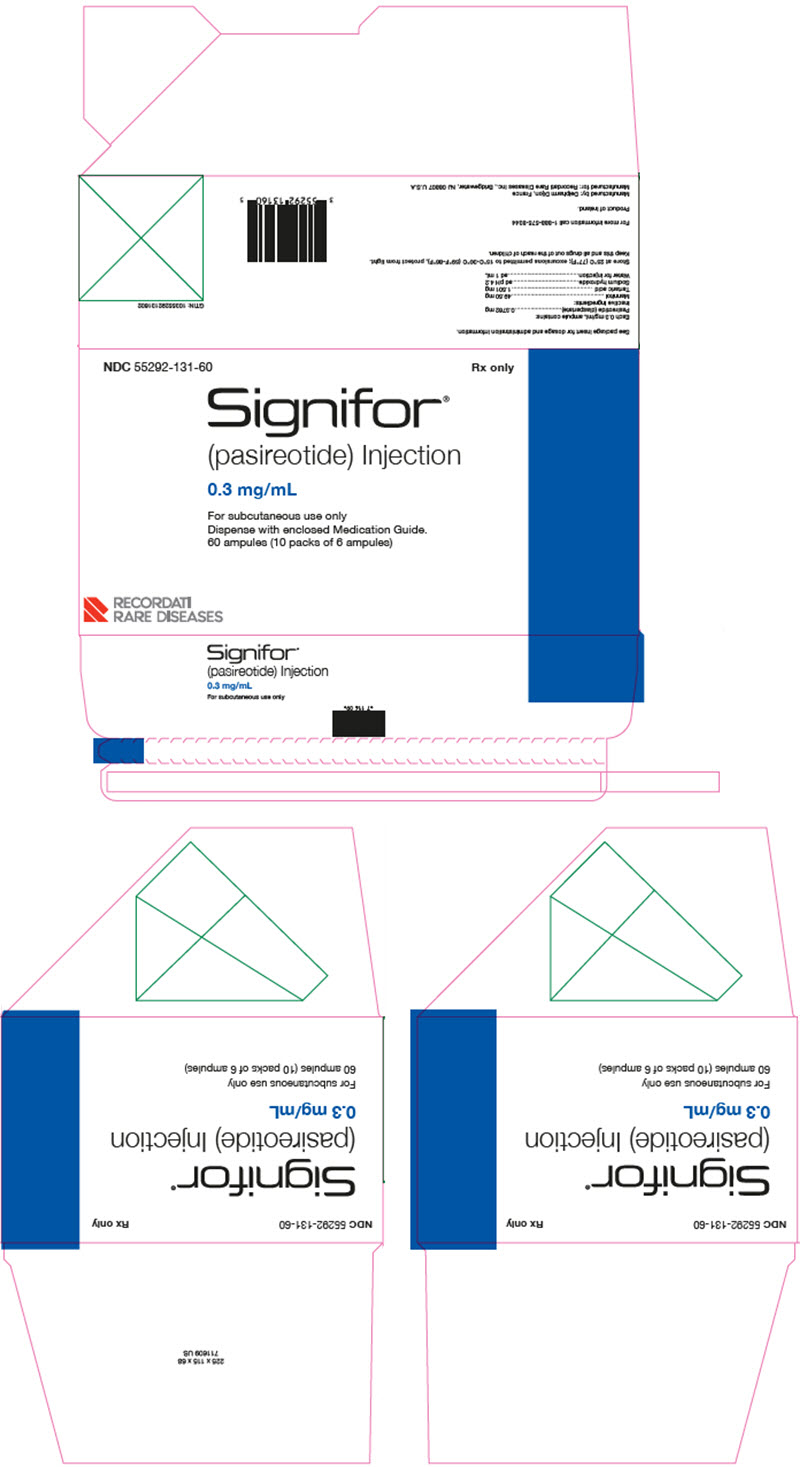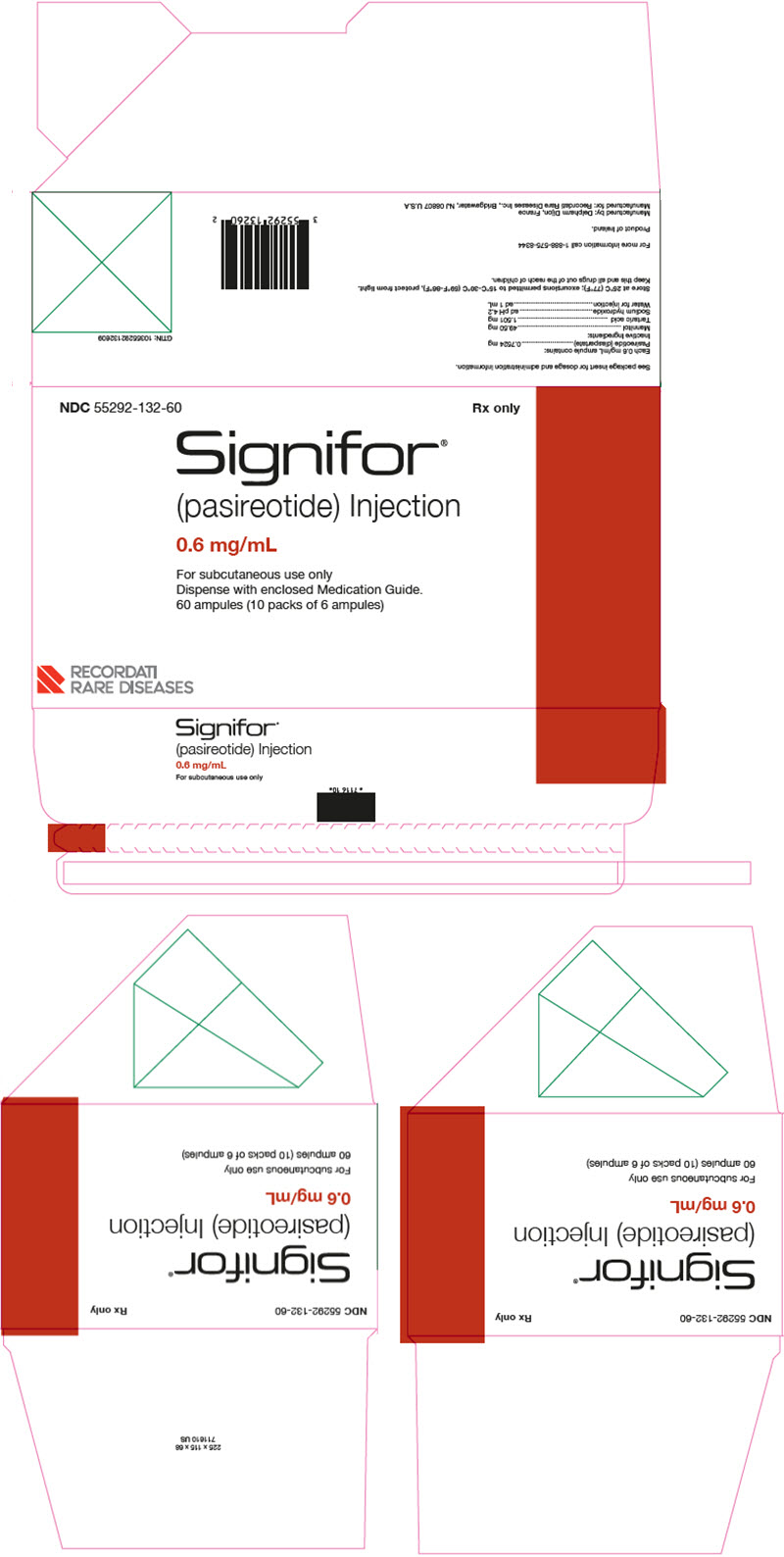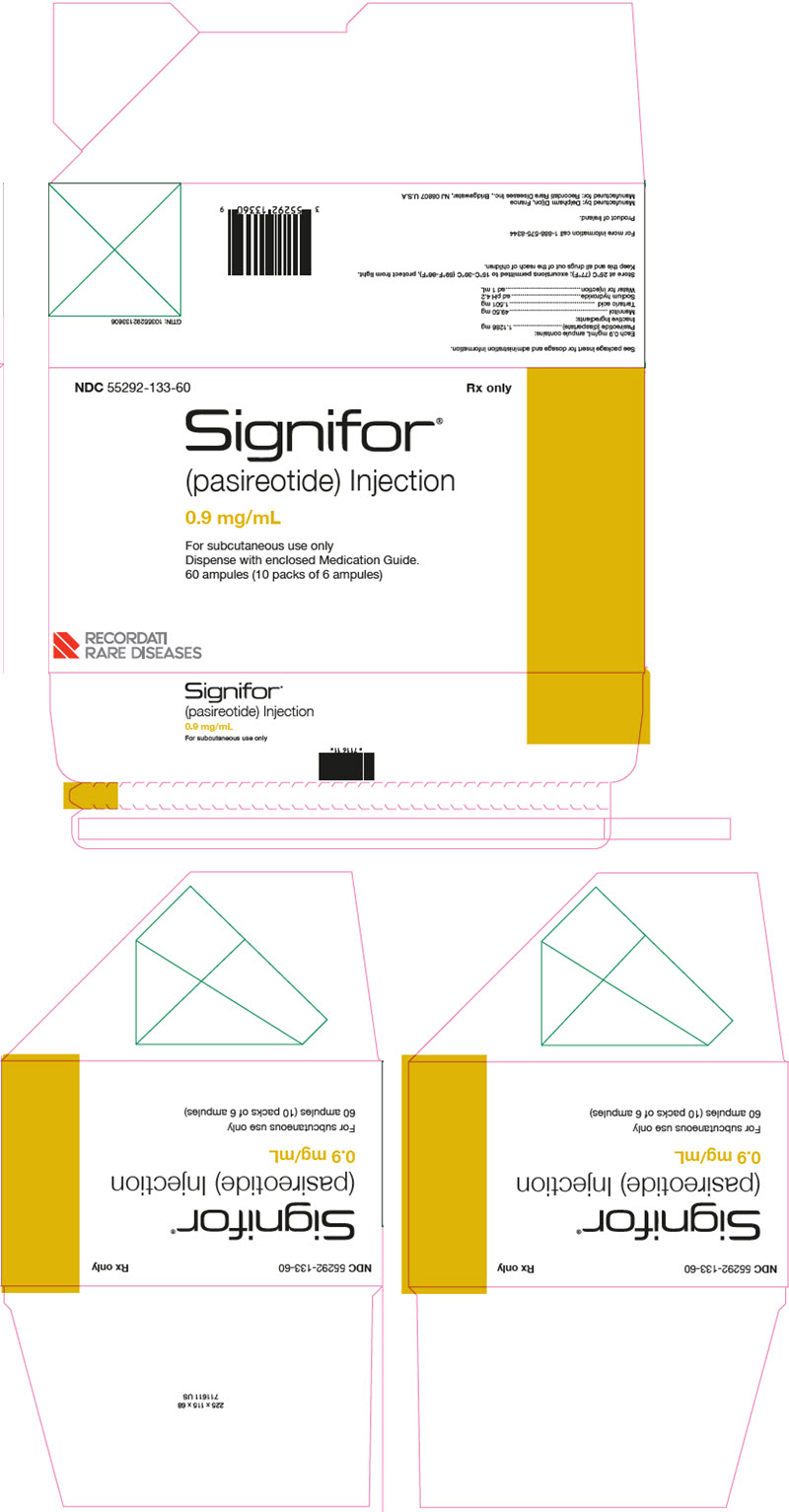 DRUG LABEL: Signifor
NDC: 55292-131 | Form: INJECTION
Manufacturer: Recordati Rare Diseases, Inc.
Category: prescription | Type: HUMAN PRESCRIPTION DRUG LABEL
Date: 20260217

ACTIVE INGREDIENTS: PASIREOTIDE 0.3 mg/1 mL
INACTIVE INGREDIENTS: MANNITOL 49.5 mg/1 mL; TARTARIC ACID 1.501 mg/1 mL; SODIUM HYDROXIDE; WATER

HIGHLIGHTS OF PRESCRIBING INFORMATION

These highlights do not include all the information needed to use SIGNIFOR safely and effectively. See full prescribing information for SIGNIFOR.
SIGNIFOR ® (pasireotide) injection, for subcutaneous use
Initial U.S. Approval: 2012

RECENT MAJOR CHANGES

Warnings and Precautions, Steatorrhea and Malabsorption of Dietary Fats (5.7) | 7/2024

1 INDICATIONS AND USAGE

SIGNIFOR is a somatostatin analog indicated for the treatment of adult patients with Cushing's disease for whom pituitary surgery is not an option or has not been curative (1)

2 DOSAGE AND ADMINISTRATION

- Recommended initial dosage is either 0.6 mg or 0.9 mg by subcutaneous injection twice a day; recommended dosage range is 0.3 mg to 0.9 mg twice a day (2.1)
- Titrate dosage based on treatment response [clinically meaningful reduction in 24-hour urinary free cortisol (UFC) and/or improvements in signs and symptoms of disease] and tolerability (2.1)
- Testing Prior to Dosing: fasting plasma glucose (FPG), hemoglobin A1c (HbA1c), liver tests, electrocardiogram (ECG), gallbladder ultrasound, and serum potassium and magnesium levels (2.2)
- Patients With Hepatic Impairment:
  - Child-Pugh B: Recommended initial dosage is 0.3 mg twice a day and maximum dosage is 0.6 mg twice a day (2.3, 8.6)
  - Child-Pugh C: Avoid use in these patients (2.3, 8.6)

3 DOSAGE FORMS AND STRENGTHS

Injection: 0.3 mg/mL, 0.6 mg/mL, and 0.9 mg/mL in a single-dose ampule (3)

4 CONTRAINDICATIONS

None (4)

5 WARNINGS AND PRECAUTIONS

- Hypocortisolism: Decreases in circulating levels of cortisol may occur resulting in biochemical and/or clinical hypocortisolism. SIGNIFOR dose reduction or interruption and/or adding a low-dose short-term glucocorticoid may be necessary (5.1)
- Hyperglycemia and Diabetes (occurs with initiation): Intensive glucose monitoring is recommended and may require initiation or adjustment of anti-diabetic treatment per standard of care (5.2)
- Bradycardia and QT Prolongation: Use with caution in at-risk patients; ECG testing prior to dosing and on treatment (5.3, 7.1)
- Liver Test Elevations: Evaluate liver tests prior to and during treatment (5.4)
- Cholelithiasis and Complications of Cholelithiasis: Monitor periodically. Discontinue if complications of cholelithiasis are suspected (5.5)
- Steatorrhea and Malabsorption of Dietary Fats: New onset steatorrhea, stool discoloration, loose stools, abdominal bloating, and weight loss may occur. If new occurrence or worsening of these symptoms are reported, evaluate for potential pancreatic exocrine insufficiency (5.7)

6 ADVERSE REACTIONS

Most common adverse reactions occurring in ≥ 20% of patients are diarrhea, nausea, hyperglycemia, cholelithiasis, headache, abdominal pain, fatigue, and diabetes mellitus (6)

To report SUSPECTED ADVERSE REACTIONS, contact Recordati Rare Diseases at 1-888-575-8344 or FDA at 1-800-FDA-1088 or www.fda.gov/medwatch.

7 DRUG INTERACTIONS

- Drugs that Prolong QT: Use with caution in patients who are at significant risk of developing QTc prolongation (5.3, 7.1)
- Cyclosporine: Consider additional monitoring (7.2)
- Bromocriptine: Consider bromocriptine dose reduction (7.2)

8 USE IN SPECIFIC POPULATIONS

- Females and Males of Reproductive Potential: Advise premenopausal females of the potential for an unintended pregnancy (8.3)
- Safety and effectiveness of SIGNIFOR in children under 18 years have not been established (8.4)

FULL PRESCRIBING INFORMATION

1 INDICATIONS AND USAGE

1.1 Cushing's Disease

SIGNIFOR is indicated for the treatment of adult patients with Cushing's disease for whom pituitary surgery is not an option or has not been curative.

2 DOSAGE AND ADMINISTRATION

2.1 Recommended Dosage Range

The recommended dosage range of SIGNIFOR is 0.3 mg to 0.9 mg by subcutaneous injection twice a day. The recommended initial dose is either 0.6 mg or 0.9 mg twice a day. Titrate dose based on response and tolerability.

Patients should be evaluated for a treatment response [clinically meaningful reduction in 24-hour urinary free cortisol (UFC) levels and/or improvement in signs or symptoms of the disease] and should continue receiving therapy with SIGNIFOR as long as benefit is derived [see Clinical Studies (14)]. Maximum UFC reduction is typically seen by two months of treatment [see Clinical Studies (14)]. For patients who are started on 0.6 mg twice a day, a dosage increase to 0.9 mg twice a day may be considered based on the response to the treatment, as long as the 0.6 mg dosage is well tolerated by the patient.

Management of suspected adverse reactions may require temporary dose reduction of SIGNIFOR. Dose reduction by 0.3 mg decrements per injection is suggested.

2.2 Recommendations Prior to Initiation of SIGNIFOR

Prior to the start of SIGNIFOR, patients should have baseline levels of the following:

- fasting plasma glucose (FPG) [see Warnings and Precautions (5.2)]
- hemoglobin A1c (HbA1c) [see Warnings and Precautions (5.2)]
- liver tests [see Warnings and Precautions (5.4)]
- serum potassium and magnesium levels [see Warnings and Precautions (5.3)]

Patients should also have a baseline electrocardiogram (ECG) and gallbladder ultrasound [see Warnings and Precautions (5.3, 5.5)].

Treatment of patients with poorly controlled diabetes mellitus should be intensively optimized with anti-diabetic therapy prior to starting SIGNIFOR [see Warnings and Precautions (5.2)].

2.3 Dosage in Patients With Hepatic Impairment

For patients with moderate hepatic impairment (Child-Pugh B), the recommended initial dosage is 0.3 mg twice a day and the maximum dosage is 0.6 mg twice a day. Avoid the use of SIGNIFOR in patients with severe hepatic impairment (Child-Pugh C) [see Use in Specific Populations (8.6)].

2.4 Important Administration Instructions

Instruct patients to:

- Refer to the FDA-approved patient labeling (Instructions for Use) for detailed administration instructions.
- Prior to injection, visually inspect the product for particulate matter and discoloration. Do not use if particulates and/or discoloration are observed.
- Avoid injection in sites showing signs of inflammation or irritation.
- Prior to injection, gently pinch the skin at the injection site and hold the needle/syringe at an angle of approximately 45 degrees.
- Administer SIGNIFOR subcutaneously by self-injection into the top of the thigh or the abdomen.
- Avoid multiple subcutaneous injections at the same site within short periods of time. Use of the same injection site for 2 consecutive injections is not recommended.
- If a dose of SIGNIFOR is missed, the next injection should be administered at the scheduled time. Do not double doses to make up for a missed dose.

3 DOSAGE FORMS AND STRENGTHS

Injection: 0.3 mg/mL, 0.6 mg/mL, and 0.9 mg/mL in a single-dose, 1 mL colorless glass ampule.

4 CONTRAINDICATIONS

None.

5 WARNINGS AND PRECAUTIONS

5.1 Hypocortisolism

Treatment with SIGNIFOR leads to suppression of adrenocorticotropic hormone (ACTH) secretion in Cushing's disease. Suppression of ACTH may lead to a decrease in circulating levels of cortisol and potentially hypocortisolism.

Monitor and instruct patients on the signs and symptoms associated with hypocortisolism (e.g., weakness, fatigue, anorexia, nausea, vomiting, hypotension, hyponatremia, or hypoglycemia). If hypocortisolism occurs, consider temporary dose reduction or interruption of treatment with SIGNIFOR, as well as temporary, exogenous glucocorticoid replacement therapy.

5.2 Hyperglycemia and Diabetes

Blood glucose elevations have been seen in healthy volunteers and patients treated with SIGNIFOR. In the clinical study [see Clinical Studies (14)], patients developed pre-diabetes and diabetes. Nearly all patients in the study, including those with normal glucose status at baseline, pre-diabetes, and diabetes, developed worsening glycemia in the first two weeks of treatment. Cushing's disease patients with poor glycemic control (HbA1c > 8%) may be at a higher risk of developing severe hyperglycemia and associated complications, e.g., ketoacidosis.

Assess the patient's glycemic status prior to starting treatment with SIGNIFOR. In patients with uncontrolled diabetes mellitus, optimize anti-diabetic therapy prior to SIGNIFOR initiation. Glycemic monitoring should be done every week for the first two to three months and periodically thereafter, as well as over the first two to four weeks after any dose increase. If hyperglycemia develops, initiate or adjust anti-diabetic treatment per standard of care. If uncontrolled hyperglycemia persists despite appropriate treatment, reduce the dose or discontinue SIGNIFOR and perform glycemic monitoring according to clinical practice. Patients who were initiated on anti-diabetic treatment as a result of SIGNIFOR require closer monitoring after discontinuation of SIGNIFOR, especially if the anti-diabetic therapy has a risk of causing hypoglycemia.

5.3 Bradycardia and QT Prolongation

Bradycardia

Bradycardia has been reported with the use of SIGNIFOR [see Adverse Reactions (6)]. Patients with cardiac disease and/or risk factors for bradycardia, such as history of clinically significant bradycardia, high-grade heart block, or concomitant use of drugs associated with bradycardia, should be carefully monitored. Dose adjustments of beta-blockers, calcium channel blockers, or correction of electrolyte disturbances may be necessary.

QT Prolongation

SIGNIFOR is associated with QT prolongation. In two thorough QT studies with SIGNIFOR, QT prolongation occurred at therapeutic and supra-therapeutic doses. SIGNIFOR should be used with caution in patients who are at significant risk of developing prolongation of QTc, such as those:

- with congenital long QT prolongation.
- with uncontrolled or significant cardiac disease, including recent myocardial infarction, congestive heart failure, unstable angina, or clinically significant bradycardia.
- on anti-arrhythmic therapy or other substances that are known to lead to QT prolongation.
- with hypokalemia and/or hypomagnesemia.

A baseline ECG is recommended prior to initiating therapy with SIGNIFOR and monitoring for an effect on the QTc interval is advisable. Hypokalemia and hypomagnesemia must be corrected prior to SIGNIFOR administration and should be monitored periodically during therapy.

5.4 Liver Test Elevations

In the Phase III trial, 5% of patients had an alanine aminotransferase (ALT) or aspartate aminotransferase (AST) level greater than 3 times the upper limit of normal (ULN). In the entire clinical development program of SIGNIFOR, there were 4 cases of concurrent elevations in ALT greater than 3 x ULN and bilirubin greater than 2 x ULN: one patient with Cushing's disease and 3 healthy volunteers [see Adverse Reactions (6)]. In these cases, total bilirubin elevations were seen either concomitantly or preceding the transaminase elevation.

Monitoring of liver tests should be done after 1- to 2 weeks on treatment, then monthly for 3 months, and every 6 months thereafter. If ALT is normal at baseline and elevations of ALT of 3-5 times the ULN are observed on treatment, repeat the test within a week or within 48 hours if exceeding 5 times ULN. If ALT is abnormal at baseline and elevations of ALT of 3 to 5 times the baseline values are observed on treatment, repeat the test within a week or sooner if exceeding 5 times ULN. Tests should be done in a laboratory that can provide same-day results. If the values are confirmed or rising, interrupt SIGNIFOR treatment and investigate for probable cause of the findings, which may or may not be SIGNIFOR-related. Serial measures of ALT, AST, alkaline phosphatase, and total bilirubin, should be done weekly, or more frequently, if any value exceeds 5 times the baseline value in case of abnormal baselines, or 5 times the ULN in case of normal baselines. If resolution of abnormalities to normal or near normal occurs, resuming treatment with SIGNIFOR may be done cautiously, with close observation, and only if some other likely cause has been found.

5.5 Cholelithiasis and Complications of Cholelithiasis

Cholelithiasis has been frequently reported in clinical studies with SIGNIFOR [see Adverse Reactions (6)]. There have been postmarketing reports of cholelithiasis (gallstones) resulting in complications, including cholecystitis or cholangitis and requiring cholecystectomy in patients taking SIGNIFOR. Ultrasonic examination of the gallbladder before, and periodically during SIGNIFOR therapy is recommended. If complications of cholelithiasis are suspected, discontinue SIGNIFOR and treat appropriately.

5.6 Monitoring for Deficiency of Pituitary Hormones

As the pharmacological activity of SIGNIFOR mimics that of somatostatin, inhibition of pituitary hormones, other than ACTH, may occur. Monitoring of pituitary function [e.g., thyroid-stimulating harmone (TSH)/free T4, GH/IGF-1] should occur prior to initiation of therapy with SIGNIFOR and periodically during treatment should be considered as clinically appropriate. Patients who have undergone transsphenoidal surgery and pituitary irradiation are particularly at increased risk for deficiency of pituitary hormones.

5.7 Steatorrhea and Malabsorption of Dietary Fats

New onset steatorrhea, stool discoloration and loose stools have been reported in patients receiving somatostatin analogs, including pasireotide products. Somatostatin analogs reversibly inhibit secretion of pancreatic enzymes and bile acids, which may result in malabsorption of dietary fats and subsequent symptoms of steatorrhea, loose stools, abdominal bloating, and weight loss. If new occurrence or worsening of these symptoms are reported in patients receiving SIGNIFOR, evaluate patients for potential pancreatic exocrine insufficiency and manage accordingly.

6 ADVERSE REACTIONS

Clinically significant adverse reactions that appear in other sections of the labeling include:

- Hypocortisolism [see Warnings and Precautions (5.1)]
- Hyperglycemia and Diabetes [see Warnings and Precautions (5.2)]
- Bradycardia and QT prolongation [see Warnings and Precautions (5.3)]
- Liver Test Elevations [see Warnings and Precautions (5.4)]
- Cholelithiasis and Complications of Cholelithiasis [see Warnings and Precautions (5.5)]
- Pituitary Hormone Deficiency [see Warnings and Precautions (5.6)]
- Steatorrhea and Malabsorption of Dietary Fats [see Warnings and Precautions (5.7)]

6.1 Clinical Trials Experience

Because clinical trials are conducted under widely varying conditions, adverse reaction rates observed in clinical trials of a drug cannot be directly compared to rates in clinical trials of another drug and may not reflect the rates observed in practice.

A total of 162 Cushing's disease patients were exposed to SIGNIFOR in the Phase III study [see Clinical Studies (14)]. At study entry, patients were randomized to receive twice a day doses of either 0.6 mg or 0.9 mg of SIGNIFOR given subcutaneously. The mean age of patients was approximately 40 years old with a predominance of female patients (78%). The majority of the patients had persistent or recurrent Cushing's disease (83%) and few patients (≤ 5%) in either treatment group had received previous pituitary irradiation. The median exposure to the treatment was 10.4 months (0.03-37.8) with 68% of patients having at least 6-months exposure.

In the Phase III trial, adverse reactions were reported in 98% of patients. The most common adverse reactions (frequency ≥ 20% in either group) were diarrhea, nausea, hyperglycemia, cholelithiasis, headache, abdominal pain, fatigue, and diabetes mellitus. There were no deaths during the study. Serious adverse events were reported in 25% of patients. Adverse events leading to study discontinuation were reported in 17% of patients.

Adverse reactions with an overall frequency higher than 5% are presented in Table 1 by randomized dose group and overall. Adverse reactions are ranked by frequency, with the most frequent reactions listed first.

Table 1 - Adverse Reactions [n (%)] With an Overall Frequency of More Than 5% in the Combined Dose Group in the Phase III Study in Cushing's Disease Patients
 | SIGNIFOR 0.6 mg twice a day N = 82 | SIGNIFOR 0.9 mg twice a day N = 80 | Overall N = 162
Diarrhea | 48 (59) | 46 (58) | 94 (58)
Nausea | 38 (46) | 46 (58) | 84 (52)
Hyperglycemia | 31 (38) | 34 (43) | 65 (40)
Cholelithiasis | 25 (30) | 24 (30) | 49 (30)
Headache | 23 (28) | 23 (29) | 46 (28)
Abdominal pain | 19 (23) | 20 (25) | 39 (24)
Fatigue | 12 (15) | 19(24) | 31 (19)
Diabetes mellitus | 13 (16) | 16 (20) | 29 (18)
Injection-site reactions | 14 (17) | 14 (18) | 28 (17)
Nasopharyngitis | 10 (12) | 11 (14) | 21 (13)
Alopecia | 10 (12) | 10 (13) | 20 (12)
Asthenia | 13 (16) | 5 (6) | 18 (11)
Glycosylated hemoglobin increased | 10 (12) | 8 (10) | 18 (11)
Alanine aminotransferase increased | 11 (13) | 6 (8) | 17 (10)
Gamma-glutamyl transferase increased | 10 (12) | 7 (9) | 17 (10)
Edema peripheral | 9 (11) | 8 (10) | 17 (10)
Abdominal pain upper | 10 (12) | 6 (8) | 16 (10)
Decreased appetite | 7 (9) | 9 (11) | 16 (10)
Hypercholesterolemia | 7 (9) | 9 (11) | 16 (10)
Hypertension | 8 (10) | 8 (10) | 16 (10)
Dizziness | 8 (10) | 7 (9) | 15 (9)
Hypoglycemia | 12 (15) | 3 (4) | 15 (9)
Type 2 diabetes mellitus | 10 (12) | 5 (6) | 15 (9)
Anxiety | 5 (6) | 9 (11) | 14 (9)
Influenza | 9 (11) | 5 (6) | 14 (9)
Insomnia | 3 (4) | 11 (14) | 14 (9)
Myalgia | 10 (12) | 4 (5) | 14 (9)
Arthralgia | 5 (6) | 8 (10) | 13 (8)
Pruritus | 6 (7) | 7 (9) | 13 (8)
Lipase increased | 7 (9) | 5 (6) | 12 (7)
Constipation | 7 (9) | 4 (5) | 11 (7)
Hypotension | 5 (6) | 6 (8) | 11 (7)
Vomiting | 3 (4) | 8 (10) | 11 (7)
Back pain | 4 (5) | 6 (8) | 10 (6)
Dry skin | 5 (6) | 5 (6) | 10 (6)
Electrocardiogram QT prolonged | 5 (6) | 5 (6) | 10 (6)
Hypokalemia | 6 (7) | 4 (5) | 10 (6)
Pain in extremity | 6 (7) | 4 (5) | 10 (6)
Sinus bradycardia | 8 (10) | 2 (3) | 10 (6)
Vertigo | 4 (5) | 6 (8) | 10 (6)
Abdominal distension | 4 (5) | 5 (6) | 9 (6)
Adrenal insufficiency | 4 (5) | 5 (6) | 9 (6)
Aspartate aminotransferase increased | 6 (7) | 3 (4) | 9 (6)
Blood glucose increased | 6 (7) | 3 (4) | 9 (6)

Other notable adverse reactions which occurred with a frequency less than 5% were: anemia (4%), blood amylase increased (2%), and prothrombin time prolonged (2%).

Gastrointestinal Disorders

Gastrointestinal disorders, predominantly diarrhea, nausea, abdominal pain, and vomiting were reported frequently in the Phase III trial (see Table 1). These events began to develop primarily during the first month of treatment with SIGNIFOR and required no intervention.

Hyperglycemia and Diabetes

Hyperglycemia-related terms were reported frequently in the Phase III trial. For all patients, these terms included: hyperglycemia (40%), diabetes mellitus (18%), increased HbA1c (11%), type 2 diabetes mellitus (9%). In general, increases in FPG and HbA1c were seen soon after initiation of SIGNIFOR and were sustained during the treatment period. In the SIGNIFOR 0.6 mg group, mean FPG levels increased from 98.6 mg/dL at baseline to 125.1 mg/dL at Month 6. In the SIGNIFOR 0.9 mg group, mean fasting FPG levels increased from 97.0 mg/dL at baseline to 128.0 mg/dL at Month 6. In the SIGNIFOR 0.6 mg group, HbA1c increased from 5.8% at baseline to 7.2% at Month 6. In the SIGNIFOR 0.9 mg group, HbA1c increased from 5.8% at baseline to 7.3% at Month 6 [see Warnings and Precautions (5.2)].

At one-month follow-up visits, following discontinuation of SIGNIFOR, mean FPG and HbA1c levels decreased but remained above baseline values. Long-term follow-up data are not available.

Elevated Liver Tests

In the Phase III trial, there were transient mean elevations in aminotransferase values in patients treated with SIGNIFOR. Mean values returned to baseline levels by Month 4 of treatment. The elevations were not associated with clinical symptoms of hepatic disease.

In the clinical development program of SIGNIFOR, there were 4 patients with concurrent elevations in ALT greater than 3 x ULN and bilirubin greater than 2 x ULN: one patient with Cushing's disease and 3 healthy volunteers [see Warnings and Precautions (5.4)]. In all 4 cases, the elevations were noted within the first 10 days of treatment. In all of these cases, total bilirubin elevations were seen either concomitantly or preceding the transaminase elevation. The patient with Cushing's disease developed jaundice. All 4 cases had resolution of the laboratory abnormalities with discontinuation of SIGNIFOR.

Hypocortisolism

Cases of hypocortisolism were reported in the Phase III study in Cushing's disease patients [see Adverse Reactions (6), Clinical Studies (14)]. The majority of cases were manageable by reducing the dose of SIGNIFOR and/or adding low-dose, short-term glucocorticoid therapy [see Warnings and Precautions (5.1)].

Injection-Site Reactions

Injection-site reactions were reported in 17% of patients enrolled in the Phase III trial in Cushing's disease. The events were most frequently reported as local pain, erythema, hematoma, hemorrhage, and pruritus. These events resolved spontaneously and required no intervention.

Thyroid Function

Hypothyroidism, with the use of SIGNIFOR, was reported for seven patients participating in the Phase III study in Cushing's disease. All seven patients presented with a TSH close to or below the lower limit at study entry, which precludes establishing a conclusive relationship between the adverse event and the use of SIGNIFOR.

Other Abnormal Laboratory Findings

Asymptomatic and reversible elevations in lipase and amylase were observed in patients receiving SIGNIFOR in clinical studies. Pancreatitis is a potential adverse reaction associated with the use of somatostatin analogs due to the association between cholelithiasis and acute pancreatitis.

For hemoglobin levels, mean decreases that remained within normal range were observed. Also, post-baseline elevations in prothrombin time (PT) and partial thromboplastin time (PTT) were noted in 33% and 47% of patients, respectively. The PT and PTT elevations were minimal.

These laboratory findings are of unclear clinical significance.

6.2 Postmarketing Experience

Additional adverse reactions have been identified during postapproval use of SIGNIFOR. Because these reactions are reported voluntarily from a population of uncertain size, it is generally not possible to reliably estimate their frequency or establish a causal relationship to drug exposure.

- Cholelithiasis resulting in complications, including cholecystitis and cholangitis, which have sometimes required cholecystectomy

7 DRUG INTERACTIONS

7.1 Effects of Other Drugs on SIGNIFOR

Drugs That Prolong QT

Coadministration of drugs that prolong the QT interval with SIGNIFOR may have additive effects on the prolongation of the QT interval. Caution is required when coadministering SIGNIFOR with drugs that may prolong the QT interval [see Warnings and Precautions (5.3)].

7.2 Effects of SIGNIFOR on Other Drugs

Cyclosporine

Concomitant administration of cyclosporine with pasireotide may decrease the relative bioavailability of cyclosporine and, therefore, dose adjustment of cyclosporine to maintain therapeutic levels may be necessary.

Bromocriptine

Coadministration of somatostatin analogues with bromocriptine may increase the blood levels of bromocriptine. Dose reduction of bromocriptine may be necessary.

8 USE IN SPECIFIC POPULATIONS

8.1 Pregnancy

Risk Summary

The limited data with SIGNIFOR in pregnant women are insufficient to inform a drug-associated risk for major birth defects and miscarriage. In embryo-fetal development studies in rabbits, findings indicating developmental delay were observed with subcutaneous administration of pasireotide during organogenesis at doses less than the exposure in humans at the highest recommended dose; maternal toxicity was not observed at this dose (see Data).

The estimated background risk of major birth defects and miscarriage for the indicated population is unknown. In the U.S. general population, the estimated background risk of major birth defects and miscarriage in clinically recognized pregnancies is 2%-4% and 15%-20%, respectively.

Data

Animal Data

In embryo-fetal development studies in rats given 1, 5, and 10 mg/kg/day subcutaneously throughout organogenesis, maternal toxicity was observed at all doses, including the lowest dose tested which had exposures 4 times higher than that at the maximum therapeutic dose based on area under the curve (AUC) comparisons across species. An increased incidence of early/total resorptions and malrotated limbs was observed in rats at 10 mg/kg/day. At 10 mg/kg/day in rats, the maternal systemic exposure (AUC) was 42179 ng*hr/mL, approximately 144 times the exposure in humans at the highest recommended dose of 900 mcg SIGNIFOR administered as a subcutaneous injection twice a day.

In embryo-fetal development studies in rabbits given 0.05, 1, and 5 mg/kg/day subcutaneously through organogenesis, maternal toxicity was observed at 1 mg/kg/day, at a maternal systemic exposure (AUC) of 1906 ng*hr/mL, approximately 7 times higher than the maximum human therapeutic exposure. An increased incidence of unossified forepaw phalanx, indicative of a developmental retardation, was observed in rabbits at 0.05 mg/kg/day, with maternal systemic exposures less than the systemic exposure in humans at the highest recommended dose.

In pre- and post-natal developmental studies in rats given subcutaneous doses of 2, 5, and 10 mg/kg/day during gestation through lactation and weaning, maternal toxicity was observed at all doses, including the lowest dose (12 times higher than the maximum therapeutic dose based on surface area comparisons across species). Retardation of physiological growth, attributed to GH inhibition was observed at 2 mg/kg/day during a pre- and post-natal study in rats. After weaning, body weight gains in the rat pups (F1 generation) exposed to pasireotide were comparable to controls, showing reversibility of this developmental delay.

8.2 Lactation

Risk Summary

There is no information available on the presence of SIGNIFOR in human milk, the effects of the drug on the breastfed infant, or the effects of the drug on milk production. Studies show that pasireotide administered subcutaneously passes into the milk of lactating rats; however, due to species-specific differences in lactation physiology, animal data may not reliably predict drug levels in human milk (see Data). The developmental and health benefits of breastfeeding should be considered along with the mother's clinical need for SIGNIFOR and any potential adverse effects on the breastfed child from SIGNIFOR or from the underlying maternal condition.

Data

Available data in animals have shown excretion of pasireotide in milk. After a single 1 mg/kg [^14C]-pasireotide subcutaneous dose to lactating rats, the transfer of radioactivity into milk was observed. The overall milk:plasma (M/P) exposure ratio of total radioactivity was 0.28, based on AUC0-∞ values.

8.3 Females and Males of Reproductive Potential

Discuss the potential for unintended pregnancy with premenopausal women as the therapeutic benefits of a reduction or normalization of serum cortisol levels in female patients with Cushing's disease treated with pasireotide may lead to improved fertility.

8.4 Pediatric Use

Safety and effectiveness of SIGNIFOR have not been established in pediatric patients.

8.5 Geriatric Use

Clinical studies of SIGNIFOR did not include sufficient numbers of patients aged 65 and over to determine whether they respond differently from younger patients. Other reported clinical experience has not identified differences in responses between the elderly and younger patients. In general, dose selection for an elderly patient should be cautious, usually starting at the low end of the dosing range, reflecting the greater frequency of decreased hepatic, renal, or cardiac function, and concomitant disease or other drug therapy [see Clinical Pharmacology (12.3)].

8.6 Hepatic Impairment

Dose adjustment is not required in patients with mild impaired hepatic function (Child-Pugh A), but is required for patients with moderately impaired hepatic function (Child-Pugh B) [see Dosage and Administration (2.3), Clinical Pharmacology (12.3)]. Avoid the use of SIGNIFOR in patients with severe hepatic impairment (Child-Pugh C).

8.7 Renal Impairment

No dosage adjustment of SIGNIFOR in patients with impaired renal function is required [see Clinical Pharmacology (12.3)].

10 OVERDOSAGE

No cases of overdosage have been reported in patients with Cushing's disease receiving SIGNIFOR subcutaneously. Doses up to 2.1 mg twice a day have been used in healthy volunteers with adverse reactions of diarrhea being observed at a high frequency.

In the event of overdosage, it is recommended that appropriate supportive treatment be initiated, as dictated by the patient's clinical status, until resolution of the symptoms.

Up-to-date information about the treatment of overdose can be obtained from a certified Regional Poison Center. Contact Poison Control (1-800-222-1222) for latest recommendations.

11 DESCRIPTION

SIGNIFOR (pasireotide) injection is prepared as a sterile solution of pasireotide diaspartate in a tartaric acid buffer for administration by subcutaneous injection. SIGNIFOR is a somatostatin analog. Pasireotide diaspartate, chemically known as (2-Aminoethyl) carbamic acid (2R,5S,8S,11S,14R,17S,19aS)-11-(4-aminobutyl)-5-benzyl-8-(4-benzyloxybenzyl)-14-(1H-indol-3-ylmethyl)-4,7,10,13,16,19-hexaoxo-17-phenyloctadecahydro-3a,6,9,12,15,18-hexaazacyclopentacyclooctadecen-2-yl ester, di[(S)-2-aminosuccinic acid] salt, is a cyclohexapeptide with pharmacologic properties mimicking those of the natural hormone somatostatin.

The molecular formula of pasireotide diaspartate is C58H66N10O9 • 2 C4H7NO4 and the molecular weight is 1313.41 g/mol. The structural formula is:

SIGNIFOR is supplied as a sterile solution in a single-dose, 1 mL colorless glass ampule containing pasireotide in 0.3 mg/mL, 0.6 mg/mL, or 0.9 mg/mL strengths for subcutaneous injection.

Each glass ampule contains:

 | 0.3 mg | 0.6 mg | 0.9 mg
Pasireotide diaspartate | 0.3762* | 0.7524* | 1.1286*
Mannitol | 49.50 | 49.50 | 49.50
Tartaric acid | 1.501 | 1.501 | 1.501
Sodium hydroxide | ad pH 4.2 | ad pH 4.2 | ad pH 4.2
Water for injection | ad 1 mL | ad 1 mL | ad 1 mL
*corresponds to 0.3/0.6/0.9 mg pasireotide base.
Note: Each ampule contains an overfill of 0.1 mL to allow accurate administration of 1 mL from the ampule.

12 CLINICAL PHARMACOLOGY

12.1 Mechanism of Action

SIGNIFOR is an injectable cyclohexapeptide somatostatin analogue. Pasireotide exerts its pharmacological activity via binding to somatostatin receptors (SSTRs). Five human somatostatin receptor subtypes are known: SSTR 1, 2, 3, 4, and 5. These receptor subtypes are expressed in different tissues under normal physiological conditions. Corticotroph tumor cells from Cushing's disease patients frequently over-express SSTR5 whereas the other receptor subtypes are often not expressed or are expressed at lower levels. Pasireotide binds and activates the SSTRs resulting in inhibition of ACTH secretion, which leads to decreased cortisol secretion.

The binding affinities of endogenous somatostatin and pasireotide are shown in Table 2.

Table 2 - Binding Affinities of Somatostatin (SRIF-14) and Pasireotide to the Five Human Somatostatin Receptor Subtypes (SSTR1-5)
Compound | SSTR1 | SSTR2 | SSTR3 | SSTR4 | SSTR5
Somatostatin (SRIF-14) | 0.93 ± 0.12 | 0.15 ± 0.02 | 0.56 ± 0.17 | 1.5 ± 0.4 | 0.29 ± 0.04
Pasireotide | 9.3 ± 0.1 | 1.0 ± 0.1 | 1.5 ± 0.3 | > 100 | 0.16 ± 0.01
Results are the mean ± SEM of IC50 values expressed as nmol/L.

12.2 Pharmacodynamics

Glucose Metabolism

In a randomized, double-blind mechanism study conducted in healthy volunteers, the development of hyperglycemia with pasireotide at doses of 0.6 mg twice a day and 0.9 mg twice a day was related to significant decreases in insulin secretion as well as incretin hormones (i.e., glucagon-like peptide-1 [GLP-1] and glucose-dependent insulinotropic polypeptide [GIP]) [see Warnings and Precautions (5.2), Adverse Reactions (6.1)].

Cardiac Electrophysiology

QTcI interval was evaluated in a randomized, blinded, crossover study in healthy subjects investigating pasireotide doses of 0.6 mg twice a day and 1.95 mg twice a day. The maximum mean (95% upper confidence bound) placebo-subtracted QTcI change from baseline was 12.7 (14.7) ms and 16.6 (18.6) ms, respectively. Both pasireotide doses decreased heart rate, with a maximum mean (95% lower confidence bound) placebo-subtracted change from baseline of -10.9 (-11.9) beats per minute (bpm) observed at 1.5 hours for pasireotide 0.6 mg twice a day, and -15.2 (-16.5) bpm at 0.5 hours for pasireotide 1.95 mg twice a day. The supra-therapeutic dose (1.95 mg twice a day) produced mean steady-state Cmax values 3.3-fold the mean Cmax for the 0.6 mg twice a day dose in the study.

12.3 Pharmacokinetics

In healthy volunteers, pasireotide demonstrates approximately linear pharmacokinetics (PK) for a dose range from 0.0025 to 1.5 mg. In Cushing's disease patients, pasireotide demonstrates linear dose-exposure relationship in a dose range from 0.3 mg to 1.2 mg.

Absorption and Distribution

In healthy volunteers, pasireotide peak plasma concentration is reached within Tmax 0.25-0.5 hour. Cmax and AUC are dose-proportional following administration of single and multiple doses.

No studies have been conducted to evaluate the absolute bioavailability of pasireotide in humans. Food effect is unlikely to occur since SIGNIFOR is administered via a parenteral route.

In healthy volunteers, pasireotide is widely distributed with large apparent volume of distribution (Vz/F > 100 L). Distribution between blood and plasma is concentration independent and shows that pasireotide is primarily located in the plasma (91%). Plasma protein binding is moderate (88%) and independent of concentration.

Pasireotide has low passive permeability and is likely to be a substrate of P-glycoprotein (P-gp), but the impact of P-gp on ADME (absorption, distribution, metabolism, excretion) of pasireotide is expected to be low. In clinical testing in healthy volunteers, P-gp inhibition (e.g., verapamil) did not affect the rate or extent of pasireotide availability. Pasireotide is not a substrate of efflux transporter BCRP (breast cancer resistance protein), influx transporter OCT1 (organic cation transporter 1), or influx transporters OATP (organic anion-transporting polypeptide) 1B1, 1B3, or 2B1.

Metabolism and Excretion

Pasireotide was shown to be metabolically stable in human liver and kidney microsomes systems. In healthy volunteers, pasireotide in its unchanged form is the predominant form found in plasma, urine, and feces. Somatropin may increase CYP450 enzymes and, therefore, suppression of growth hormone secretion by somatostatin analogs, including pasireotide may decrease the metabolic clearance of compounds metabolized by CYP450 enzymes.

Pasireotide is eliminated mainly via hepatic clearance (biliary excretion) with a small contribution of the renal route. In a human ADME study 55.9 ± 6.63% of the radioactivity dose was recovered over the first 10 days post dosing, including 48.3 ± 8.16% of the radioactivity in feces and 7.63 ± 2.03% in urine.

The clearance (CL/F) of pasireotide in healthy volunteers and Cushing's disease patients is ~7.6 L/h and ~3.8 L/h, respectively.

Steady-State Pharmacokinetics

Following multiple subcutaneous doses, pasireotide demonstrates linear pharmacokinetics in the dose range of 0.05 to 0.6 mg once a day in healthy volunteers, and 0.3 mg to 1.2 mg twice a day in Cushing's disease patients. Based on the accumulation ratios of AUC, the calculated effective half-life (t1/2,eff) in healthy volunteers was approximately 12 hours (on average between 10 and 13 hours for 0.05, 0.2 and 0.6 mg once a day doses).

Specific Populations

Population PK analyses of SIGNIFOR indicate that race, body weight, age, and gender do not have a clinically relevant influence on PK parameters. No dose adjustment is required for demographics.

Hepatic Impairment

In a clinical study with a single subcutaneous dose of 600 mcg pasireotide in subjects with impaired hepatic function (Child-Pugh A, B, and C), subjects with moderate and severe hepatic impairment (Child-Pugh B and C) showed significantly higher exposures than subjects with normal hepatic function. Upon comparison with the control group, AUCinf was increased by 12%, 56%, and 42%; and Cmax increased by 3%, 46%, and 33%, respectively, in the mild, moderate, and severe hepatic impairment groups [see Use in Specific Populations (8.6), Dosage and Administration (2.3)].

Pediatric Patients

No studies have been performed in pediatric patients [see Use in Specific Populations (8.4)].

Geriatric Patients

No clinical pharmacology studies have been performed in geriatric patients.

Renal Impairment

Renal clearance has a minor contribution to the elimination of pasireotide in humans. In a clinical study with a single subcutaneous dose of 900 mcg pasireotide, in subjects with impaired renal function, renal impairment of mild, moderate, or severe degree or end stage renal failure, did not have a significant impact on the pharmacokinetics of pasireotide [see Use in Specific Populations (8.7)].

Drug Interaction Studies

There was no significant drug interaction between pasireotide and metformin, nateglinide or liraglutide.

13 NONCLINICAL TOXICOLOGY

13.1 Carcinogenesis, Mutagenesis, Impairment of Fertility

Carcinogenesis

A life-time carcinogenicity study was conducted in rats and transgenic mice. Rats were given daily subcutaneous doses of pasireotide at 0.01, 0.05, 0.3 mg/kg/day for 104 weeks. There were no drug-related tumors in rats at exposures up to 7-fold higher than the maximum recommended clinical exposure at the 1.8 mg/day dose. Mice were given subcutaneous doses of pasireotide at 0.5, 1.0, 2.5 mg/kg/day for 26 weeks and did not identify any carcinogenic potential.

Mutagenesis

Pasireotide was not genotoxic in a battery of in vitro assays (Ames mutation test in Salmonella and Escherichia coli and mutation test in human peripheral lymphocytes). Pasireotide was not genotoxic in an in vivo rat bone marrow nucleus test.

Impairment of Fertility

Subcutaneous dosing at 0.1 mg/kg/day before mating and continuing into gestation in rats at exposures less than the human clinical exposure based on body surface area comparisons across species resulted in statistically significant increased implantation loss and decreased viable fetuses, corpora lutea, and implantation sites. Abnormal cycles or acyclicity were observed at 1 mg/kg/day (5-fold higher than the maximum therapeutic exposure based on surface area, comparisons across species).

14 CLINICAL STUDIES

A Phase III, multicenter, randomized study was conducted to evaluate the safety and efficacy of two dose levels of SIGNIFOR over a 6-month treatment period in Cushing's disease patients with persistent or recurrent disease despite pituitary surgery or de novo patients for whom surgery was not indicated or who had refused surgery.

Patients with a baseline 24-hour urine free cortisol (UFC) >1.5 x ULN were randomized to receive a SIGNIFOR dosage of either 0.6 mg subcutaneous twice a day or 0.9 mg subcutaneous twice a day. After 3 months of treatment, patients with a mean 24-hour UFC ≤ 2.0 x ULN and below or equal to their baseline values continued blinded treatment at the randomized dose until Month 6. Patients who did not meet these criteria were unblinded and the dose was increased by 0.3 mg twice a day. After the initial 6 months in the study, patients entered an additional 6-month open-label treatment period. The dosage could be reduced by 0.3 mg twice a day at any time during the study for intolerability.

A total of 162 patients were enrolled in this study. The majority of patients were female (78%) and had persistent or recurrent Cushing's disease despite pituitary surgery (83%) with a mean age of 40 years. A few patients (4%) in either treatment group received previous pituitary irradiation. The median value of the baseline 24-hour UFC for all patients was 565 nmol/24 hours (normal range 30 to 145 nmol/24 hours). About two-thirds of all randomized patients completed 6 months of treatment.

The primary efficacy endpoint was the proportion of patients who achieved normalization of mean 24-hour UFC levels after 6 months of treatment and did not dose increase during this period.

24-Hour Urinary Free Cortisol Results

At Month 6, the percentages of responders for the primary endpoint were 15% and 26% in the 0.6 mg twice a day and 0.9 mg twice a day groups, respectively (Table 3). The percentages of patients with mUFC ≤ ULN or ≥ 50% reduction from baseline, a less stringent endpoint than the primary endpoint, were 34% in the 0.6 mg twice a day and 41% in the 0.9 mg twice a day groups. Dose increases appeared to have minimal effect on 24-hour UFC response. Mean and median percentage changes in UFC from baseline are presented in Table 3.

Table 3 – 24-Hour Urinary Free Cortisol Study Results at Month 6 in Patients With Cushing's Disease
 | SIGNIFOR 0.6 mg twice a day N = 82 | SIGNIFOR 0.9 mg twice a day N = 80
UFC Responders n/N % (95% CI) | 12/82 15% (7%, 22%) | 21/80 26% (17%, 36%)
UFC Levels (nmol/24 hr) Baseline Mean (SD) Median | N = 78 868 (764) 704 | N = 72 750 (930) 470
% Change from baseline Mean (95% CI) Median | -22% (-44%, +1%) -47% | -42% (-50%, -33%) -46%

SIGNIFOR resulted in a decrease in the mean 24-hour UFC after 1 month of treatment (Figure 1). For patients (n = 78) who stayed in the trial, similar UFC lowering was observed at Month 12.

Figure 1 – Mean (± SE) Urinary Free Cortisol (nmol/24h) at Time Points up to Month 6 by Randomized Dose Group

Note: Only patients who completed 6 months of treatment are included in this analysis (n = 110). The reference line is the ULN for UFC, which is 145 nmol/24hour; +/-Standard errors are displayed.

Other Endpoints

Decreases from baseline for blood pressure were observed at Month 6, including patients who did not receive any anti-hypertensive medication. However, due to the fact that the study allowed initiation of anti-hypertensive medication and dose increases in patients already receiving such medications, the individual contribution of SIGNIFOR or of anti-hypertensive medication adjustments cannot be clearly established.

The mean decreases from baseline at Month 6 for weight, body mass index, and waist circumference were 4.4 kg, 1.6 kg/m^2 and 2.6 cm, respectively. Individual patients showed varying degrees of improvement in Cushing's disease manifestations, but because of the variability in response and the absence of a control group in this trial, it is uncertain whether these changes could be ascribed to the effects of SIGNIFOR.

16 HOW SUPPLIED/STORAGE AND HANDLING

SIGNIFOR is supplied as a single dose, colorless glass ampule packaged in a box of 60 ampules, arranged in 10 packs of 6 ampules each. The following packaging configurations are available.

0.3 mg/1 mL pasireotide (as diaspartate)

Box of 60 ampules NDC# 55292-131-60

0.6 mg/1 mL pasireotide (as diaspartate)

Box of 60 ampules NDC# 55292-132-60

0.9 mg/1 mL pasireotide (as diaspartate)

Box of 60 ampules NDC# 55292-133-60

Store at 25°C (77°F); excursions permitted to 15°C-30°C (59°F-86°F), protect from light.

17 PATIENT COUNSELING INFORMATION

See FDA approved patient labeling (Medication Guide and Instructions for Use).

Counsel patients on the following possible significant adverse reactions:

- Hypocortisolism [see Warnings and Precautions (5.1)]
- Hyperglycemia and Diabetes [see Warnings and Precautions (5.2)]
- Bradycardia and QT Prolongation [see Warnings and Precautions (5.3)]
- Liver Test elevations [see Warnings and Precautions (5.4)]
- Cholelithiasis and Complications of Cholelithiasis: Advise patients to contact their healthcare provider if they experience signs or symptoms of gallstones (cholelithiasis) or complications of gallstones (e.g., cholecystitis or cholangitis) [see Warnings and Precautions (5.5)]
- Pituitary Hormone Deficiency [see Warnings and Precautions (5.6)]
- Steatorrhea and Malabsorption of Dietary Fats: Advise patients to contact their healthcare provider if they experience new or worsening symptoms of steatorrhea, stool discoloration, loose stools, abdominal bloating, and weight loss [see Warnings and Precautions (5.7)]
- Pregnancy: Inform female patients that treatment with SIGNIFOR may result in unintended pregnancy [see Use in Specific Populations (8.3)]

Instruct the patients on the proper use of SIGNIFOR, including instructions to:

- Carefully review the Medication Guide.
- Do not reuse unused portions of SIGNIFOR ampules and properly dispose of the ampules after use.
- Avoid multiple injections at or near the same site within short periods of time.

For instructions on the use of SIGNIFOR glass ampules, refer to the Medication Guide that follows.

Manufactured for:
Recordati Rare Diseases Inc., Bridgewater, NJ 08807 U.S.A

Medication Guide
SIGNIFOR® [sig-na-for]
(pasireotide)
Injection

Read this Medication Guide before you start using SIGNIFOR and each time you get a refill. There may be new information. This information does not take the place of talking to your doctor about your medical condition or your treatment.

What is the most important information I should know about SIGNIFOR?

SIGNIFOR can cause serious side effects, including:

- Low cortisol levels in your blood (hypocortisolism). Tell your doctor right away if you have any signs and symptoms of hypocortisolism. Signs and symptoms of hypocortisolism may include:
  - weakness
  - fatigue
  - loss of appetite
  - nausea
  - vomiting
  - low blood pressure
  - low level of sodium in your blood
  - low blood sugar
  If you get hypocortisolism while taking SIGNIFOR, your doctor may change your dose or ask you to stop taking it.

- High blood sugar (hyperglycemia). Your doctor should check your blood sugar level before you start taking SIGNIFOR and while you take it. Signs and symptoms of hyperglycemia may include:
  - excessive thirst
  - high urine output
  - increased appetite with weight loss
  - tiredness
  If you get hyperglycemia while taking SIGNIFOR, your doctor may give you another medicine to take to lower your blood sugar. Your doctor may also change your dose of SIGNIFOR or ask you to stop taking it.

What is SIGNIFOR?

SIGNIFOR is a prescription medicine used to treat Cushing's disease in adults who cannot have surgery or have failed surgery.

It is not known if SIGNIFOR is safe and effective in children.

What should I tell my doctor before using SIGNIFOR?

Before you take SIGNIFOR, tell your doctor if you:

- have or have had high blood sugar (hyperglycemia)
- have diabetes
- have or have had heart problems
- have a history of low levels of potassium or magnesium in your blood
- have or have had liver problems
- have or have had gallstones
- have any other medical conditions
- are pregnant or plan to become pregnant. SIGNIFOR may harm your unborn baby.
- are breastfeeding or plan to breastfeed. It is not known if SIGNIFOR passes into your breast milk. You and your doctor should decide if you will take SIGNIFOR or breastfeed. You should not do both.

Tell your doctor about all the medicines you take, including prescription and non-prescription medicines, vitamins, and herbal supplements.

Taking SIGNIFOR with certain other medicines can affect each other and cause side effects. Especially tell your doctor if you take:

- medicines to control your heart beat (anti-arrhythmics)
- medicines that can affect the electrical system of your heart (QT prolongation)
- medicines to control your blood pressure (such as beta-blockers or calcium channel blockers)
- medicines to control the electrolyte (such as potassium or magnesium) levels in your blood
- cyclosporine (Gengraf ®, Neoral ®, Restasis ®, Sandimmune ®)
- bromocriptine (Cycloset ®, Parlodel ®)

Ask your doctor for a list of these medicines, if you are not sure.

Know the medicines you take. Keep a list of them to show to your doctor and pharmacist when you get a new medicine.

How should I use SIGNIFOR?

- Read the "Instructions for Use" at the end of this Medication Guide for information about the right way to use SIGNIFOR.
- Use SIGNIFOR exactly as your doctor tells you to.
- Your doctor may change your dose if needed.
- Before you use SIGNIFOR for the first time, your doctor should do a blood test to check your blood sugar levels and your liver tests.
- Before you use SIGNIFOR for the first time, your doctor should do a test to check your heart (electrocardiogram) and your gallbladder (ultrasound).
- SIGNIFOR should be clear and colorless. Before you inject your dose, check to make sure that SIGNIFOR is clear and colorless, and does not have any clumps or particles in it.
- SIGNIFOR is given as an injection into the fat just under your skin (subcutaneous injection).
- Do not inject SIGNIFOR into skin that is red or irritated.
- The recommended injection sites for SIGNIFOR are the top of your thigh or stomach area (abdomen).
- Change (rotate) your injection site with each dose. Do not inject SIGNIFOR into the exact same spot for each injection.
- Your doctor should show you how to prepare and give your dose of SIGNIFOR before you use it for the first time.
- You should not inject SIGNIFOR until your doctor has shown you how to use it the right way.

If you take too much SIGNIFOR, tell your doctor right away.

What are the possible side effects of SIGNIFOR?

SIGNIFOR may cause serious side effects, including:

- See "What is the most important information I should know about SIGNIFOR?"
  - slow heart rate (bradycardia). SIGNIFOR can cause your heart to beat slower, which may cause you to feel weak, dizzy or even faint. People who have, or have had, heart problems are at higher risk for bradycardia.
  - problems with the electrical system of your heart (QT interval prolongation), which can put you at risk for abnormal heart beats, dizziness, and fainting spells that can be very serious. Call your doctor right away if you experience such spells.
  - elevation of your liver tests. Your doctor should do blood tests to monitor your liver tests while you use SIGNIFOR.
  - gallstones (cholelithiasis) and complications that can happen if you have gallstones. Gallstones are a serious but common side effect of SIGNIFOR. Possible complications of gallstones include inflammation and infection of the gallbladder. Your doctor should do a test (ultrasound) to check for gallstones before you start using SIGNIFOR and while you use it.
    Tell your healthcare provider if you get any of these symptoms.
  - fatty stool. SIGNIFOR may cause your body to have issues absorbing dietary fats. Tell your doctor if you have any new or worsening symptoms including fatty stools, changes in the color of your stools, loose stools, stomach (abdominal) bloating or weight loss.
    - sudden pain in your upper right stomach area (abdomen)
    - yellowing of your skin and whites of your eyes
    - nausea
    - sudden pain in your right shoulder or between your shoulder blades
    - fever with chills

The most common side effects of SIGNIFOR include:

- diarrhea
- nausea
- high blood sugar
- headache
- abdominal pain
- fatigue
- diabetes mellitus
- injection-site reactions
- common cold
- hair loss
- weakness
- fluid retention
- Abnormal blood test result for glycosylated hemoglobin (the level of glycosylated hemoglobin indicates the average blood sugar level over the previous months)

Tell your doctor if you have any side effect that bothers you or that does not go away.

These are not all the possible side effects of SIGNIFOR. For more information, ask your doctor or pharmacist.

Call your doctor for medical advice about side effects. You may report side effects to FDA at 1–800–FDA–1088.

How should I store SIGNIFOR?

- Store SIGNIFOR at 68°F to 77°F (20°C to 25°C).
- Keep SIGNIFOR out of the light.

Keep SIGNIFOR and all medicines out of the reach of children.

General information about the safe and effective use of SIGNIFOR.

Medicines are sometimes prescribed for purposes other than those listed in a Medication Guide. Do not use SIGNIFOR for a condition for which it was not prescribed. Do not give SIGNIFOR to other people, even if they have the same symptoms that you have. It may harm them.

This Medication Guide summarizes the most important information about SIGNIFOR. If you would like more information, talk to your doctor. You can ask your pharmacist or doctor for information about SIGNIFOR that is written for health professionals.

For more information go to www.SIGNIFOR.com or call 1-888-575-8344.

What are the ingredients in SIGNIFOR?

Active ingredient: Pasireotide

Inactive ingredients: Mannitol, sodium hydroxide, tartaric acid, and water for injection.

This Medication Guide has been approved by the U.S. Food and Drug Administration.

Revised: 7/2024

Instructions for Use

SIGNIFOR® [sig-na-for]

(pasireotide)

Injection

Supplies you will need to give your SIGNIFOR injection:

- 1 SIGNIFOR ampule (See Figure A)
- 1 sterile syringe (See Figure B)
- 1 long sterile needle (See Figure B)
  - This needle is used to draw up your SIGNIFOR from the ampule. You should only use this needle if your doctor or nurse tells you to.
- 1 short sterile needle (See Figure B)
- Alcohol wipes
- 1 cotton ball or gauze
- A sharps disposal container or other closeable, puncture resistant disposal container

Getting started:

Step 1: Wash your hands well with soap and water and dry them.

Step 2: Take 1 SIGNIFOR ampule out of the box.

Step 3: Look at the SIGNIFOR ampule. Check that the ampule is not cracked or broken and that the liquid medicine in the ampule is clear and colorless.

Do not use SIGNIFOR if the ampule is cracked or broken or if the liquid looks cloudy or contains particles. Take the whole box back to the pharmacy and get a new one.

Ampules should be opened just prior to administration and any unused portion discarded.

Step 4: Check the dose and expiration date printed on the ampule (See Figure C).

Preparing your SIGNIFOR dose:

Step 5: Hold the SIGNIFOR ampule at the bottom with 1 hand. With your other hand, tap the top of the SIGNIFOR ampule with your finger to make sure there is no liquid in the top of the ampule when you open it (See Figure D).

Figure D

Step 6: Hold the ampule with 1 hand. With your other hand, hold the top of the ampule and pull it sideways until the top snaps off at the line marked on the ampule neck (See Figure E).

- Put the ampule upright on a clean and flat surface.

Figure E

Step 7: Open the sterile needle package. Place the needle on the top of the syringe. Push down on the needle and twist it clockwise until it is tight (See Figure F).

- If you have been told to use 1 long and 1 short needle, you should use the long needle for this step.

Figure F

Step 8: Pull the needle cover straight off the sterile needle (See Figure G).

Figure G

Step 9: Put the needle into the ampule making sure you do not touch the outside of the ampule and pull up on the plunger to draw up all of the SIGNIFOR liquid into the syringe (See Figure H).

- If you have been told to use 1 long and 1 short needle, you should now take the long needle off of the syringe and put on the short one.

Figure H

Step 10: Hold the syringe upright in 1 hand between 2 fingers with your thumb at the bottom of the plunger. With your other hand, tap the syringe with your finger to get rid of air bubbles (See Figure I).

Figure I

Step 11: Push up on the plunger until you see a drop of liquid on the tip of the needle (See Figure J).

- Do not let the needle touch anything. You are now ready to inject your dose of SIGNIFOR.

Figure J

Injecting your SIGNIFOR dose:

Step 12: Choose your injection site and wipe the site with an alcohol wipe (See Figure K). Let the site dry.

Figure K

Step 13: With 1 hand, gently pinch the skin at the injection site you have chosen and wiped with an alcohol wipe. With your other hand, pick up the syringe and hold it like a pencil. Insert the needle into the pinched skin at a 45 degree angle using a quick dart like motion (See Figure L).

- Do not let go of the skin.

Figure L

Step 14: Gently press the plunger all the way down, until the syringe is empty (See Figure M).

Figure M

Step 15: When the syringe is empty, slowly let go of the skin and gently pull the needle out of the skin (See Figure N).

Figure N

Step 16: Place a cotton ball or gauze over the injection site and press for about 5 seconds. Do not massage the injection site.

- If there is bleeding, cover it with a bandage.

After injecting your SIGNIFOR dose:

- Put your used needles and syringes in a FDA-cleared sharps disposal container right away after use. Do not throw away (dispose of) loose needles and syringes in your household trash.
  - If you do not have a FDA-cleared sharps disposal container, you may use a household container that is:
    - made of a heavy-duty plastic,
    - can be closed with a tight-fitting, puncture-resistant lid, without sharps being able to come out,
    - upright and stable during use,
    - leak-resistant, and
    - properly labeled to warn of hazardous waste inside the container.
  - When your sharps disposal container is almost full, you will need to follow your community guidelines for the right way to dispose of your sharps disposal container. There may be state or local laws about how you should throw away used needles and syringes. For more information about safe sharps disposal, and for specific information about sharps disposal in the state that you live in, go to the FDA's website at: http://www.fda.gov/safesharpsdisposal.
  - Do not dispose of your used sharps disposal container in your household trash unless your community guidelines permit this. Do not recycle your used sharps disposal container.

This Instructions for Use has been approved by the U.S. Food and Drug Administration. Revised: July 2024

Manufactured for:

Recordati Rare Diseases Inc., Bridgewater, NJ 08807 U.S.A

PRINCIPAL DISPLAY PANEL - 0.3 mg/mL Ampule Package Box

NDC 55292-131-60
Rx only

Signifor®
(pasireotide) Injection

0.3 mg/mL

For subcutaneous use only
Dispense with enclosed Medication Guide.
60 ampules (10 packs of 6 ampules)

RECORDATI
RARE DISEASES

PRINCIPAL DISPLAY PANEL - 0.6 mg/mL Ampule Package Box

NDC 55292-132-60
Rx only

Signifor®
(pasireotide) Injection

0.6 mg/mL

For subcutaneous use only
Dispense with enclosed Medication Guide.
60 ampules (10 packs of 6 ampules)

RECORDATI
RARE DISEASES

PRINCIPAL DISPLAY PANEL - 0.9 mg/mL Ampule Package Box

NDC 55292-133-60
Rx only

Signifor®
(pasireotide) Injection

0.9 mg/mL

For subcutaneous use only
Dispense with enclosed Medication Guide.
60 ampules (10 packs of 6 ampules)

RECORDATI
RARE DISEASES